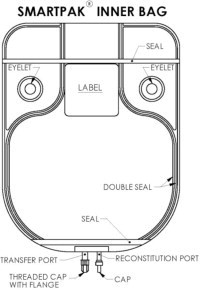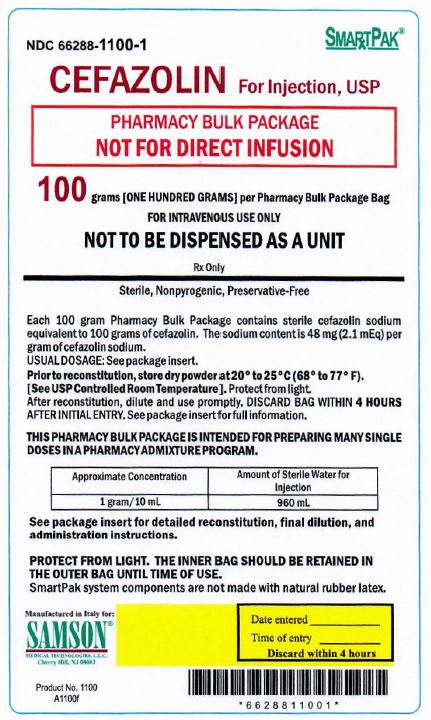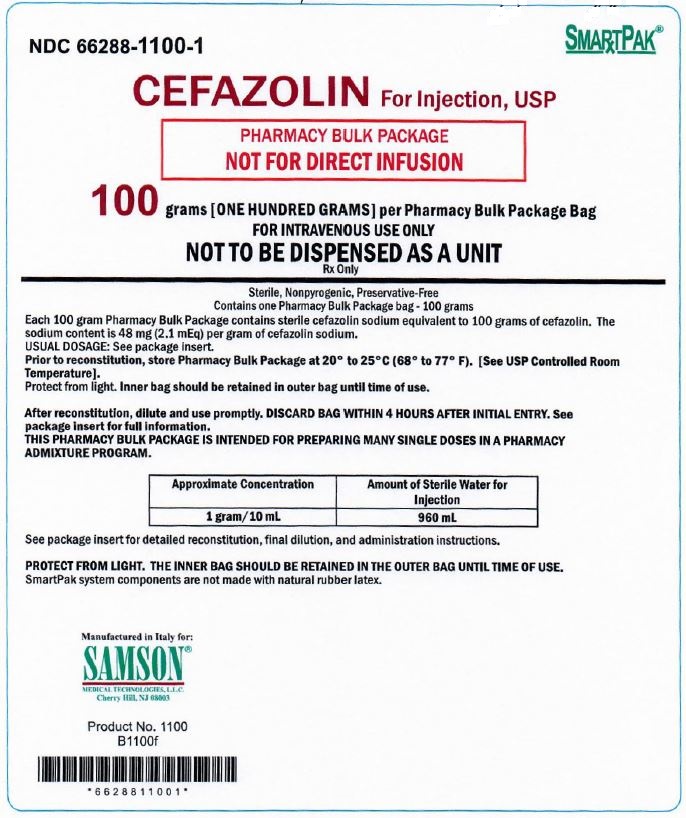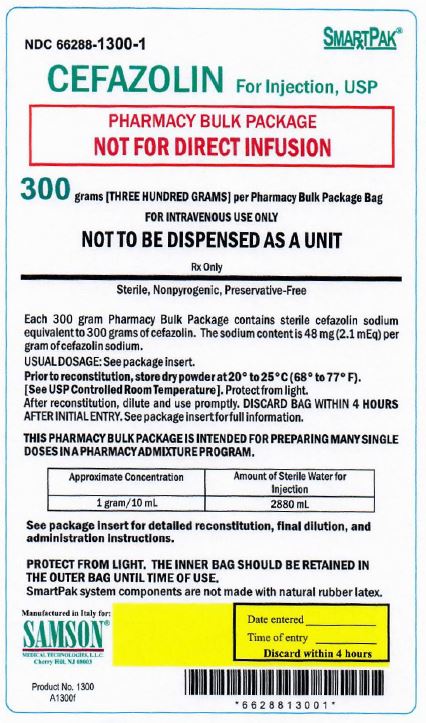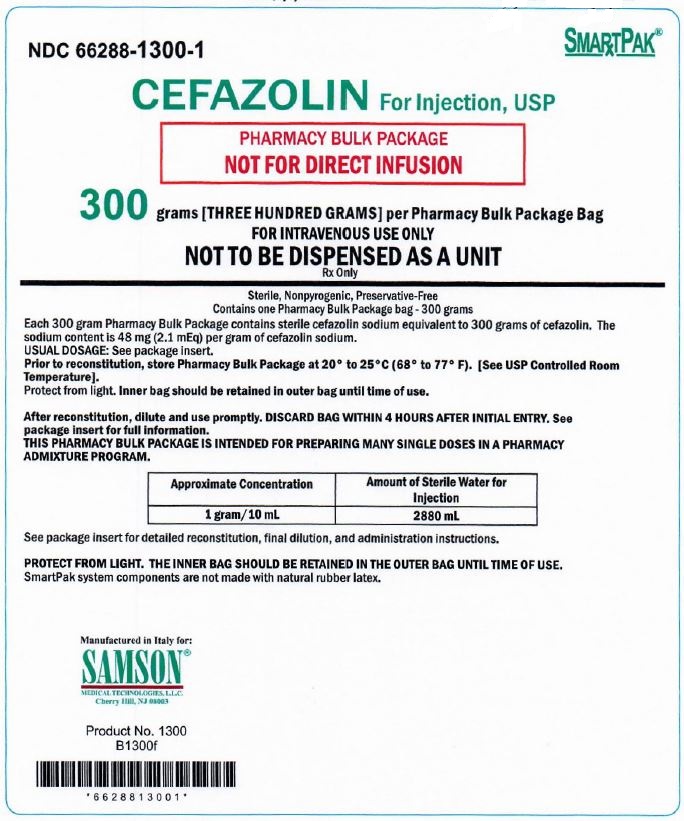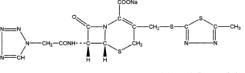 DRUG LABEL: CEFAZOLIN
NDC: 66288-1100 | Form: INJECTION, POWDER, LYOPHILIZED, FOR SOLUTION
Manufacturer: Samson Medical Technologies, L.L.C.
Category: prescription | Type: HUMAN PRESCRIPTION DRUG LABEL
Date: 20250108

ACTIVE INGREDIENTS: Cefazolin Sodium 100 g/1 1

HIGHLIGHTS OF PRESCRIBING INFORMATION

These highlights do not include all the information needed to use Cefazolin for Injection, USP safely and effectively. See full prescribing information for Cefazolin for Injection, USP.
CEFAZOLIN FOR INJECTION, USP
Initial U.S. Approval: 1973

1 INDICATIONS AND USAGE

Cefazolin for Injection, USP is a cephalosporin antibacterial indicated in the treatment of the following infections caused by susceptible isolates of the designated microorganisms: Respiratory tract infections (1.1); urinary tract infections (1.2); skin and skin structure infections (1.3); biliary tract infections (1.4); bone and joint infections (1.5); genital infections (1.6); septicemia (1.7); endocarditis (1.8); and perioperative prophylaxis (1.9).

2 DOSAGE AND ADMINISTRATION

For intravenous use only over approximately 30 minutes. (2)

THIS IS A PHARMACY BULK PACKAGE NOT FOR DIRECT INJECTION.

Cefazolin for Injection USP, Pharmacy Bulk Package bag SmartPak® should not be used in patients who require less than a 250 mg dose of cefazolin (2.1)

Recommended Dosing Schedule in Adult Patients with CrCl Greater Than or Equal to 55 mL/min (2.1)
Site and Type of Infection | Dose | Frequency
Moderate to severe infections | 500 mg to 1 gram | Every 6 to 8 hours
Mild infections caused by susceptible gram-positive cocci | 250 mg to 500 mg | Every 8 hours
Acute, uncomplicated urinary tract infections | 1 gram | Every 12 hours
Pneumococcal pneumonia | 500 mg | Every 12 hours
Severe, life-threatening infections (e.g., endocarditis, septicemia)* | 1 gram to 1.5 grams | Every 6 hours
Perioperative prophylaxis | 1 gram to 2 grams | ½ to 1 hour prior to start of surgery
Perioperative prophylaxis | 500 mg to 1 gram | During surgery for lengthy procedures
Perioperative prophylaxis | 500 mg to 1 gram | Every 6 to 8 hours for 24 hours postoperatively
*In rare instances, doses of up to 12 grams of cefazolin per day have been used.
Cefazolin for Injection USP, Pharmacy Bulk Package bag SmartPak® should not be used in patients who require less than a 250 mg dose of cefazolin (2.1)

3 DOSAGE FORMS AND STRENGTHS

Pharmacy Bulk Package bags, 100 grams and 300 grams (3)

THIS IS A PHARMACY BULK PACKAGE – NOT FOR DIRECT INJECTION

4 CONTRAINDICATIONS

Hypersensitivity to cefazolin or other cephalosporin class antibacterial drugs, penicillins or other beta-lactams (4.1)

5 WARNINGS AND PRECAUTIONS

- Hypersensitivity reactions: Cross-hypersensitivity may occur in up to 10% of patients with a history of penicillin allergy. If an allergic reaction occurs, discontinue the drug. (5.1)
- Use in patients with renal impairment: Cefazolin for Injection USP, Pharmacy Bulk Package bag SmartPak® should not be used in patients who require less than a 250 mg dose of cefazolin: Dose adjustment required for patients with CrCl less than 55 mL/min. (5.2)
- Clostridium difficile-associated diarrhea: May range from mild diarrhea to fatal colitis. Evaluate if diarrhea occurs. (5.3)

6 ADVERSE REACTIONS

Most common adverse reactions: gastrointestinal (nausea, vomiting, diarrhea) and allergic reactions (anaphylaxis, urticaria, skin rash). (6)

To report SUSPECTED ADVERSE REACTIONS, contact Samson Medical Technologies, L.L.C. at 1-877-418-3600 or FDA at 1-800-FDA-1088 or www.fda.gov/medwatch

7 DRUG INTERACTIONS

Probenecid may decrease renal tubular secretion of cephalosporins when used concurrently, resulting in increased and more prolonged cephalosporin blood concentrations. (7)

8 USE IN SPECIFIC POPULATIONS

- Pediatric Use: Cefazolin for Injection USP – Pharmacy Bulk Package bag, SmartPak® should not be used in pediatric patients who require less than a 250 mg dose of cefazolin. (8.4)
- Renal Impairment: Cefazolin for Injection USP – Pharmacy Bulk Package bag SmartPak® should not be used in renally impaired patients who require less than a 250 mg dose of cefazolin. Lower daily dosage of Cefazolin for Injection is required in patients with impaired renal function (creatinine clearance less than 55 mL/min.) (8.6)

12.4 Microbiology

PHARMACY BULK PACKAGE -
NOT FOR DIRECT INFUSION

To reduce the development of drug-resistant bacteria and maintain the effectiveness of cefazolin and other antibacterial drugs, cefazolin should be used only to treat or prevent infections that are proven or strongly suspected to be caused by bacteria. (12.4)

FULL PRESCRIBING INFORMATION

1 INDICATIONS AND USAGE

To reduce the development of drug-resistant bacteria and maintain the effectiveness of cefazolin and other antibacterial drugs, cefazolin should be used only to treat or prevent infections that are proven or strongly suspected to be caused by susceptible bacteria. When culture and susceptibility information are available, they should be considered in selecting or modifying antibacterial therapy. In the absence of such data, local epidemiology and susceptibility patterns may contribute to the empiric selection of therapy.

Cefazolin for Injection is indicated for the treatment of the following infections when caused by susceptible bacteria.

1.1 Respiratory Tract Infections

Respiratory tract infections due to Streptococcus pneumoniae, Staphylococcus aureus and Streptococcus pyogenes.

Injectable benzathine penicillin is considered the drug of choice in treatment and prevention of streptococcal infections, including the prophylaxis of rheumatic fever.

Cefazolin is effective in the eradication of streptococci from the nasopharynx; however, data establishing the efficacy of cefazolin in the subsequent prevention of rheumatic fever are not available.

1.2 Urinary Tract Infections

Urinary tract infections due to Escherichia coli and Proteus mirabilis.

1.3 Skin and Skin Structure Infections

Skin and skin structure infections due to S. aureus, S. pyogenes, and Streptococcus agalactiae.

1.4 Biliary Tract Infections

Biliary infections due to E. coli, various isolates of streptococci, P. mirabilis, and S. aureus.

1.5 Bone and Joint Infections

Bone and joint infections due to S. aureus.

1.6 Genital Infections

Genital infections due to E. coli and P. mirabilis.

1.7 Septicemia

Septicemia due to S. pneumoniae, S. aureus, P. mirabilis, and E. coli.

1.8 Endocarditis

Endocarditis due to S. aureus and S. pyogenes.

1.9 Perioperative Prophylaxis

The prophylactic administration of cefazolin preoperatively, intraoperatively, and postoperatively may reduce the incidence of certain postoperative infections in patients undergoing surgical procedures which are classified as contaminated or potentially contaminated (e.g., vaginal hysterectomy, and cholecystectomy in high-risk patients such as those older than 70 years, with acute cholecystitis, obstructive jaundice, or common duct bile stones).

The perioperative use of cefazolin may also be effective in surgical patients in whom infection at the operative site would present a serious risk (e.g., during open-heart surgery and prosthetic arthroplasty).

If there are signs of infection, specimens for cultures should be obtained for the identification of the causative organism so that appropriate therapy may be instituted.

2 DOSAGE AND ADMINISTRATION

Cefazolin for Injection USP, Pharmacy Bulk Package bag SmartPak® should not be used in patients who require less than a 250 mg dose of Cefazolin.

THIS PHARMACY BULK PACKAGE REQUIRES RECONSTITUTION WITH STERILE WATER FOR INJECTION, USP TO A CONCENTRATION OF 100 mg per mL AND FURTHER DILUTION IN 50 mL OF A COMPATIBLE SOLUTION.

THIS IS A PHARMACY BULK PACKAGE - NOT FOR DIRECT INJECTION

2.1 Adult Population

Cefazolin for Injection USP, Pharmacy Bulk Package bag SmartPak® should not be used in patients who require less than a 250 mg dose of Cefazolin.

Cefazolin for Injection should be reconstituted with Sterile Water for Injection, USP to a concentration of 100 mg per mL and further diluted in 50 mL of a compatible solution. The recommended adult dosages are outlined in Table 1. Cefazolin for Injection should be administered intravenously (IV) over approximately 30 minutes.

Table 1: Recommended Dosing Schedule in Adult Patients with CrCl Greater Than or Equal to 55 mL/min.
Site and Type of Infection | Dose | Frequency
Moderate to severe infections | 500 mg to 1gram | Every 6 to 8 hours
Mild infections caused by susceptible gram-positive cocci | 250 mg to 500 mg | Every 8 hours
Acute, uncomplicated urinary tract infections | 1 gram | Every 12 hours
Pneumococcal pneumonia | 500 mg | Every 12 hours
Severe, life- threatening infections (e.g., endocarditis, septicemia)* | 1 gram to 1.5 grams | Every 6 hours
*In rare instances, doses up to 12 grams of cefazolin per day have been used.

2.2 Perioperative Prophylactic Use

Cefazolin for Injection USP, Pharmacy Bulk Package bag SmartPak® should not be used in patients who require less than a 250 mg dose of cefazolin.

To prevent postoperative infection in contaminated or potentially contaminated surgery, recommended doses are:

- 1 gram to 2 grams I.V. administered ½ hour to 1 hour prior to the start of surgery.
- For lengthy operative procedures (e.g., 2 hours or more), 500 mg to 1 gram I.V. during surgery (administration modified depending on the duration of the operative procedure).
- 500 mg to 1 gram I.V. every 6 to 8 hours for 24 hours postoperatively.

It is important that (i) the preoperative dose be given just (½ to 1 hour) prior to the start of surgery so that adequate antibacterial concentrations are present in the serum and tissues at the time of initial surgical incision; and (ii) cefazolin may be administered, if necessary, at appropriate intervals during surgery to provide sufficient concentrations of the antibacterial drug at the anticipated moments of greatest exposure to infective organisms. The prophylactic administration of cefazolin should usually be discontinued within a 24-hour period after the surgical procedure. In surgery where the occurrence of infection may be particularly devastating (e.g., open-heart surgery and prosthetic arthroplasty), the prophylactic administration of cefazolin may be continued for 3 to 5 days following the completion of surgery.

2.3 Patients with Renal Impairment

Cefazolin for Injection USP, Pharmacy Bulk Package bag SmartPak® should not be used in patients with renal impairment who require less than a 250 mg dose of cefazolin. Cefazolin may be used in patients with renal impairment with the dosage adjustments outlined in Table 2. All reduced dosage recommendations apply after an initial loading dose appropriate to the severity of the infection.

Table 2: Dosage Adjustment for Patients with Renal Impairment
Creatinine Clearance | Dose | Frequency
55 mL/minute or greater | Full dose | Normal frequency
35 to 54 mL/minute | Full dose | Every 8 hours or longer
11 to 34 mL/minute | ½ usual dose | Every 12 hours
10 mL/minute or less | ½ usual dose | Every 18 to 24 hours

2.4 Preparation for Use of Cefazolin for Injection, USP bag SmartPak® Pharmacy Bulk Package

Cefazolin for Injection USP, Pharmacy Bulk Package bag SmartPak® should not be used in patients who require less than a 250 mg dose of cefazolin.

Directions for Proper Use of a Pharmacy Bulk Package

- NOT FOR DIRECT INFUSION. The Pharmacy Bulk Package is for use in the hospital pharmacy admixture service only in a suitable work area, such as a laminar flow hood. Using aseptic technique, the container closure may be penetrated only one time after reconstitution using a suitable sterile dispensing set or transfer device that allows measured dispensing of the contents. Use of a syringe and needle is not recommended as it may cause leakage. The withdrawal of container contents should be accomplished without delay. However, should this not be possible, a maximum time of 4 HOURS from initial reconstitution port closure entry is permitted to complete fluid transfer operations. This time limit should begin with the introduction of the solvent or diluent into the Pharmacy Bulk Package. Discard any unused portion after 4 HOURS. This pharmacy bulk package is not intended to be dispensed as a unit.
- PRIOR TO RECONSTITUTION: DO NOT USE THE INNER BAG IF PARTICULATE OR FOREIGN MATTER IS PRESENT, IF THE DRY POWDER IS DARK YELLOW OR BROWN, IF THE SEALS ARE NOT INTACT, OR IF THERE IS ANY OTHER DAMAGE TO THE BAG. IN SUCH CASES, DISCARD THE BAG IMMEDIATELY.
- After initial reconstitution port entry, use entire contents of the Pharmacy Bulk Package promptly. Any unused portion must be discarded after 4 HOURS.
- Gather the following items prior to the reconstitution of the product: Appropriate number of bags of Sterile Water for Injection and, depending upon the method of filling, appropriate sterile tubing and adapters.

INSTRUCTION FOR RECONSTITUTION OF THE PHARMACY BULK PACKAGE BAG SmartPak®

The entire contents of the bag and the preparation process (reconstitution and dilution) should be completed within 4 hours of initial entry.

- Document the date and time reconstitution starts in the designated place on the container label. The entire contents of the bag must be used within 4 hours from the time of initial entry.
- Remove the translucent unthreaded cap from the reconstitution (smaller) port and discard it.
- Reconstitute the powder through the reconstitution (smaller) port, using Sterile Water for Injection according to the table below

Reconstitution Table
SmartPak® Bag Size | Amount of Sterile Water | Approximate Concentration
100 grams | 960 mL | 100 mg/mL (1 g/10 mL)
300 grams | 2880 mL | 100 mg/mL (1 g/10 mL)

- After reconstitution is complete, remove the transfer needle from the reconstitution port.
- Place the bag on a flat surface of a laminar flow hood and mix for at least 15 minutes for the 100 gram product or 25 minutes for the 300 gram product by rocking gently from side to side. CAUTION: To avoid possible leakage caused by the heavy weight of the added water, do not shake vigorously or pull strongly on the bag.
- When foam dissipates, visually inspect the bag to verify the solution is clear, colorless to pale yellow and free of particulate matter. DO NOT USE THE INNER BAG IF PARTICULATE OR FOREIGN MATTER IS PRESENT.
- Unscrew the clear threaded cap from the transfer (larger) port and discard it. Attach sterile tubing and filling adapter unit to the transfer port.
- Reconstituted solution can now be transferred using the transfer port and the filling adapter.

It should be noted that the spike placed into the transfer port of the Pharmacy Bulk Package SmartPak® is NEVER removed during this procedure and that the reconstitution port is self-sealing.

Dilution

- Hang the bag from two eyelets.
- Following reconstitution, transfer 10 mL of the reconstituted solution into transfusion bags, each containing 50 mL of one of the compatible solutions below.

Compatible solutions for dilution are the following:

Sodium Chloride Injection, USP
5% Detrose Injection, USP

- Dilution should be completed within the 4 hour preparation process.
- When diluted according to the instructions above, cefazolin is stable for 24 hours at room temperature or for 10 days if stored under refrigeration (5°C or 41°F).

Administration

Prior to administration, parenteral drug products should be inspected visually for particulate matter and discoloration whenever solution and container permit.

3 DOSAGE FORMS AND STRENGTHS

- 100 grams Cefazolin for Injection, USP, Pharmacy Bulk Package bag SmartPak®
- 300 grams Cefazolin for Injection, USP, Pharmacy Bulk Package bag SmartPak®

THIS IS A PHARMACY BULK PACKAGE – NOT FOR DIRECT INJECTION

4 CONTRAINDICATIONS

4.1 Hypersensitivity to Cefazolin or the Cephalosporin Class of Antibacterial Drugs, Penicillins or Other Beta-lactams

Cefazolin for Injection, USP is contraindicated in patients who have a history of immediate hypersensitivity reactions (e.g., anaphylaxis, serious skin reactions) to cefazolin or the cephalosporin class of antibacterial drugs, penicillins or other beta-lactams [see Warnings and Precautions (5.1)].

5 WARNINGS AND PRECAUTIONS

5.1 Hypersensitivity Reactions to Cefazolin, Cephalosporins, Penicillins or Other Beta-lactams

Serious and occasionally fatal hypersensitivity (anaphylactic) reactions have been reported in patients receiving beta-lactam antibacterial drugs. Before therapy with Cefazolin for Injection, USP is instituted, careful inquiry should be made to determine whether the patient has had previous immediate hypersensitivity reactions to cefazolin, cephalosporins, penicillins, or carbapenems. Exercise caution if this product is to be given to penicillin-sensitive patients because cross-hypersensitivity among beta-lactam antibacterial drugs has been clearly documented and may occur in up to 10% of patients with a history of penicillin allergy. If an allergic reaction to Cefazolin for Injection, USP occurs, discontinue the drug.

5.2 Use in Patients with Renal Impairment

Cefazolin for Injection USP – Pharmacy Bulk Package bags SmartPak® should not be used in renally impaired patients who require less than a 250 mg dose of cefazolin.

As with other beta-lactam antibacterial drugs, seizures may occur if inappropriately high doses are administered to patients with impaired renal function (creatinine clearance less than 55 mL/minute) [see Dosage and Administration (2.3)].

5.3 Clostridium difficile-associated Diarrhea

Clostridium difficile associated diarrhea (CDAD) has been reported with the use of nearly all antibacterial agents, including cefazolin and may range in severity from mild diarrhea to fatal colitis. Treatment with antibacterial agents alters the normal flora of the colon leading to overgrowth of C. difficile.

C. difficile produces toxins A and B, which contribute to the development of CDAD. Hypertoxin- producing isolates of C. difficile cause increased morbidity and mortality, as these infections can be refractory to antimicrobial therapy and may require colectomy. CDAD must be considered in all patients who present with diarrhea following antibacterial drug use. Careful medical history is necessary since CDAD has been reported to occur over two months after the administration of antibacterial agents.

If CDAD is suspected or confirmed, ongoing antibacterial drug use not directed against C. difficile may need to be discontinued. Appropriate fluid and electrolyte management, protein supplementation, antibacterial drug treatment of C. difficile, and surgical evaluation should be instituted as clinically indicated.

5.4 Risk of Development of Drug-resistant Bacteria

Prescribing Cefazolin for Injection, USP in the absence of proven or strongly suspected bacterial infection or a prophylactic indication is unlikely to provide benefit to the patient and increases the risk of the development of drug-resistant bacteria.

As with other antimicrobials, prolonged use of Cefazolin for Injection, USP may result in overgrowth of nonsusceptible microorganisms. Repeated evaluation of the patient's condition is essential. Should superinfection occur during therapy, appropriate measures should be taken.

5.5 Drug/Laboratory Test Interactions

Urinary Glucose

The administration of cefazolin may result in a false-positive reaction with glucose in the urine when using CLINITEST® tablets. It is recommended that glucose tests based on enzymatic glucose oxidase reactions (e.g., CLINISTIX®) be used.

Coombs' Test

Positive direct Coombs tests have been reported during treatment with cefazolin, In hematologic studies or in transfusion-cross-matching procedures when antiglobulin tests are performed on the minor side or in Coombs' testing of newborns whose mothers have received cephalosporin antibacterial drugs before parturition, it should be recognized that a positive Coombs' test may be due to the drug.

6 ADVERSE REACTIONS

The following serious adverse reactions to cefazolin are described below and elsewhere in the labeling:

- Hypersensitivity reactions [See Warnings and Precautions (5.1)]
- Clostridium difficile-associated diarrhea [see Warnings and Precautions (5.3)]

6.1 Clinical Trials Experience

The following adverse reactions were reported from clinical trials:

Gastrointestinal: Diarrhea, oral candidiasis (oral thrush), mouth ulcers, vomiting, nausea, stomach cramps, epigastric pain, heartburn, flatus, anorexia, and pseudomembranous colitis. Onset of pseudomembranous colitis symptoms may occur during or after antibacterial treatment [see Warnings and Precautions (5.3)].

Allergic: Anaphylaxis, eosinophilia, urticaria, itching, drug fever, skin rash, Stevens-Johnson syndrome.

Hematologic: Neutropenia, leukopenia, thrombocytopenia, thrombocythemia.

Hepatic: Transient rise in SGOT, SGPT, and alkaline phosphatase levels has been observed. As with other cephalosporins, reports of hepatitis have been received.

Renal: As with other cephalosporins, reports of increased BUN and creatinine levels, as well as renal failure, have been received.

Local Reactions: Instances of phlebitis have been reported at site of injection. Some induration has occurred.

Other Reactions: Pruritus (including genital, vulvar and anal pruritus, genital moniliasis, and vaginitis). Dizziness, fainting, lightheadedness, confusion, weakness, tiredness, hypotension, somnolence and headache.

6.2 Cephalosporin-class Adverse Reactions

In addition to the adverse reactions listed above that have been observed in patients treated with cefazolin, the following adverse reactions and altered laboratory tests have been reported for cephalosporin-class antibacterials: Stevens-Johnson syndrome, erythema multiforme, toxic epidermal necrolysis, renal impairment, toxic nephropathy, aplastic anemia, hemolytic anemia, hemorrhage, hepatic impairment including cholestasis and pancytopenia.

7 DRUG INTERACTIONS

Probenecid may decrease renal tubular secretion of cephalosporins when used concurrently, resulting in increased and more prolonged cephalosporin blood levels.

8 USE IN SPECIFIC POPULATIONS

8.1 Pregnancy

Pregnancy Category B.

Reproduction studies have been performed in rats, mice, and rabbits at doses of 2000, 4000 and 240 mg/kg/day or 1-3 times the maximum recommended human dose on a body surface area basis. There was no evidence of impaired fertility or harm to the fetus due to cefazolin.

8.2 Labor and Delivery

When cefazolin has been administered prior to caesarean section, drug concentrations in cord blood have been approximately one quarter to one third of maternal drug levels. The drug appears to have no adverse effect on the fetus.

8.3 Nursing Mothers

Cefazolin is present in very low concentrations in the milk of nursing mothers. Caution should be exercised when cefazolin is administered to a nursing woman.

8.4 Pediatric Use

Cefazolin for Injection USP, Pharmacy Bulk Package bag, SmartPak® should not be used in pediatric patients who require less than a 250 mg adult of cefazolin.

8.5 Geriatric Use

Of the 920 subjects who received cefazolin in clinical studies, 313 (34%) were 65 years and over, while 138 (15%) were 75 years and over. No overall differences in safety or effectiveness were observed between these subjects and younger subjects. Other reported clinical experience has not identified differences in responses between the elderly and younger patients, but greater sensitivity of some older individuals cannot be ruled out.

This drug is known to be substantially excreted by the kidney, and the risk of toxic reactions to this drug may be greater in patients with impaired renal function. Because elderly patients are more likely to have decreased renal function, care should be taken in dose selection, and it may be useful to monitor renal function [see Dosage and Administration (2.3) and Warnings and Precautions (5.2)].

8.6 Patients with Renal Impairment

Cefazolin for Injection USP, Pharmacy Bulk Package bag, SmartPak® should not be used in patients with renal impairment who require less than a 250 mg dose of Cefazolin. When cefazolin is administered to patients with low urinary output because of impaired renal function (creatinine clearance less than 55 mL/minute), lower daily dosage is required [see Dosage and Administration (2.3) and Warnings and Precautions (5.2)].

11 DESCRIPTION

Cefazolin for Injection USP, Pharmacy Bulk Package bag SmartPak® should not be used in patients who require less than a 250 mg dose of cefazolin.

Cefazolin for Injection, USP, is a sterile, lyophilized, semisynthetic cephalosporin for intravenous administration. It is the sodium salt of 3-{[(5-methyl-1,3,4-thiadiazol-2-yl)thio]-methyl}-8-oxo-7- [2-(1H -tetrazol-1-yl)acetamido]-5-thia-1-azabicyclo [4.2.0]oct-2-ene-2-carboxylic acid. Each Pharmacy Bulk Package contains 48 mg (2.1 mEq) of sodium per 1 gram of cefazolin sodium. Cefazolin for Injection, USP, is supplied in 100 grams and 300 grams SmartPak® Pharmacy Bulk Packages bags equivalent. Each SmartPak® Pharmacy Bulk Package bag contains cefazolin sodium equivalent to 100 grams or 300 grams of cefazolin.

BEFORE ADMINISTRATION, THIS PHARMACY BULK PACKAGE REQUIRES RECONSTITUTION USING STERILE WATER FOR INJECTION, USP TO A CONCENTRATION OF 100 mg per mL AND FURTHER DILUTION IN 50 mL OF A COMPATIBLE SOLUTION AND INFUSED INTRAVENOUSLY.

A Pharmacy Bulk Package is a container of a sterile preparation for intravenous use that contains many single doses. The contents are intended for use in a pharmacy admixture service and are restricted to the preparation of admixtures for intravenous infusion.

The molecular formula is C14H13N8NaO4S3. The molecular weight is 476.49.

The structural formula is as follows:

The pH of the reconstituted solution is between 4 and 6.

12 CLINICAL PHARMACOLOGY

12.1 Mechanism of Action

Cefazolin is an antibacterial drug [see Microbiology (12.4)].

12.2 Pharmacodynamics

The pharmacokinetic/pharmacodynamic relationship for cefazolin has not been evaluated in patients.

12.3 Pharmacokinetics

Studies have shown that following intravenous administration of cefazolin to normal volunteers, mean serum concentrations peaked at approximately 185 mcg/mL and were approximately 4 mcg/mL at 8 hours for a 1 gram dose.

The serum half-life for cefazolin is approximately 1.8 hours following IV administration.

In a study, using normal volunteers, of constant intravenous infusion with dosages of 3.5 mg/kg for 1 hour (approximately 250 mg) and 1.5 mg/kg the next 2 hours (approximately 100 mg), cefazolin produced a steady serum level at the third hour of approximately 28 mcg/mL.

Plasma pharmacokinetic parameters of cefazolin in normal volunteers (N=12) following a single 15-minute intravenous infusion of 2 grams of Cefazolin for Injection, USP are summarized in Table 3.

Table 3: Mean (Standard Deviation) Plasma Pharmacokinetic Parameters of Cefazolin in Normal Volunteers
 | N | Cmax (mcg/mL) | Tmax* (h) | AUC 0-inf (mcg*h/mL) | t½ (h) | CL (L/h) | Vz (L)
Single 2 g Dose as a 15-Minute I.V. Infusion | 12 | 280.9 (45.9) | 0.25 (0.25-0.33) | 509.9 (89.3) | 2.01 (0.28) | 4.03 (0.68) | 11.5 (1.53)
*Tmax reported as median(range)
N = number of subjects observed; Cmax = maximum plasma concentration; Tmax = time to maximum plasma concentration; AUC0-inf = area under the plasma concentration-time curve extrapolated to infinity; t½ = apparent plasma terminal elimination half-life; CL = total clearance; Vz = volume of distribution

Studies in patients hospitalized with infections indicate that cefazolin produces mean peak serum levels approximately equivalent to those seen in normal volunteers.

Bile levels in patients without obstructive biliary disease can reach or exceed serum levels by up to five times; however, in patients with obstructive biliary disease, bile levels of cefazolin are considerably lower than serum levels (< 1.0 mcg/mL).

In synovial fluid, the cefazolin concentration becomes comparable to that reached in serum at about 4 hours after drug administration.

Studies of cord blood show prompt transfer of cefazolin across the placenta. Cefazolin is present in very low concentrations in the milk of nursing mothers.

Cefazolin is excreted unchanged in the urine. In the first 6 hours approximately 60% of the drug is excreted in the urine and this increases to 70% to 80% within 24 hours.

12.4 Microbiology

Mechanism of Action

Cefazolin is a bactericidal agent that acts by inhibition of bacterial cell wall synthesis.

Resistance

Predominant mechanisms of bacterial resistance to cephalosporins include the presence of extended-spectrum beta-lactamases and enzymatic hydrolysis.

Antimicrobial Activity

Cefazolin has been shown to be active against most isolates of the following microorganisms both in vitro and in clinical infections as described in the INDICATIONS AND USAGE (1) section.

- Gram-Positive Bacteria
  - Staphylococcus aureus
  - Staphylococcus epidermidis
  - Streptococcus agalactiae
  - Streptococcus pneumoniae
  - Streptococcus pyogenes

Methicillin-resistant staphylococci are uniformly resistant to cefazolin,

- Gram-Negative Bacteria
  - Escherichia coli
  - Proteus mirabilis

Most isolates of indole positive Proteus (Proteus vulgaris), Enterobacter spp., Morganella morganii, Providencia rettgeri, Serratia spp. and Pseudomonas spp. are resistant to cefazolin.

Susceptibility Testing

For specific information regarding susceptibility test interpretive criteria and associated test methods and quality control standards recognized by FDA for this drug, please see: https://www.fda.gov/STIC

13 NONCLINICAL TOXICOLOGY

13.1 Carcinogenesis, Mutagenesis, Impairment of Fertility

Mutagenicity studies and long-term studies in animals to determine the carcinogenic potential of Cefazolin for Injection, USP have not been performed.

16 HOW SUPPLIED/STORAGE AND HANDLING

Cefazolin for Injection, USP, is available in the following SmartPak® Pharmacy Bulk Packages bags:

100 grams* One Pharmacy Bulk Package bag Product No. 1100 NDC 66288-1100-1

300 grams** One Pharmacy Bulk Package bag Product No. 1300 NDC 66288-1300-1

*Each 100 gram Pharmacy Bulk Package bag contains sterile cefazolin sodium equivalent to 100 grams of cefazolin.

**Each 300 gram Pharmacy Bulk Package bag contains sterile cefazolin sodium equivalent to 300 grams of cefazolin.

SmartPak® system components are not made with natural rubber latex.

As with other cephalosporins, cefazolin tends to darken depending on storage conditions within the stated recommendations; however, product potency is not adversely affected.

Storage Conditions

Prior to reconstitution, store dry powder at 20° to 25° C (68° to77° F). [See USP Controlled Room Temperature]. Protect From Light.

17 PATIENT COUNSELING INFORMATION

Patients should be advised that allergic reactions, including serious allergic reactions could occur and that serious reactions require immediate treatment and discontinuation of cefazolin. Patients should report to their health care provider any previous allergic reactions to cefazolin, cephalosporins, penicillins or other similar antibacterials.

Patients should be advised that diarrhea is a common problem caused by antibiotics, which usually ends when the antibiotic is discontinued. Sometimes after starting treatment with antibacterials, patients can develop watery and bloody stools (with or without stomach cramps and fever) even as late as two or more months after having taken the last dose of the antibacterials. If this occurs, patients should contact a physician as soon as possible.

Patients should be counseled that antibacterial drugs including cefazolin, should only be used to treat bacterial infections. They do not treat viral infections (e.g., the common cold). When cefazolin is prescribed to treat a bacterial infection, patients should be told that although it is common to feel better early in the course of therapy, the medication should be taken exactly as directed. Skipping doses or not completing the full course of therapy may: (1) decrease the effectiveness of the immediate treatment, and (2) increase the likelihood that bacteria will develop resistance and will not be treatable by cefazolin or other antibacterial drugs in the future.

Rx only
SmartPak is a registered trademark of Samson Medical Technologies, L.L.C.
Clinitest is a registered trademark of Siemens Medical Solutions Diagnostics.
Clinistix is a registered trademark of Bayer Healthcare LLC.

C1100i

Manufactured for

SAMSON MEDICAL TECHNOLOGIES, L.L.C.

Cherry Hill, NJ 08003

by

ACS Dobfar S.p.A.

20067 Tribiano (Milano) Italy

Principal Display Panel – 100 g Inner Bag Label

NDC 66288-1100-1 SMARTPAK®

CEFAZOLIN For Injection, USP

PHARMACY BULK PACKAGE
NOT FOR DIRECT INFUSION

100 grams [ONE HUNDRED GRAMS] per Pharmacy Bulk Package Bag

FOR INTRAVENOUS USE ONLY

NOT TO BE DISPENSED AS A UNIT

Rx Only

Principal Display Panel – 100 g Outer Bag Label

NDC 66288-1100-1 SMARTPAK®

CEFAZOLIN For Injection, USP

PHARMACY BULK PACKAGE
NOT FOR DIRECT INFUSION

100 grams [ONE HUNDRED GRAMS] per Pharmacy Bulk Package Bag

FOR INTRAVENOUS USE ONLY

NOT TO BE DISPENSED AS A UNIT

Rx Only

Principal Display Panel – 300 g Inner Bag Label

NDC 66288-1300-1 SMARTPAK®

CEFAZOLIN For Injection, USP

PHARMACY BULK PACKAGE

NOT FOR DIRECT INFUSION

300 grams [THREE HUNDRED GRAMS] per Pharmacy Bulk Package Bag

FOR INTRAVENOUS USE ONLY

NOT TO BE DISPENSED AS A UNIT

Rx Only

Principal Display Panel – 300 g Outer Bag Label

NDC 66288-1300-1 SMARTPAK®

CEFAZOLIN For Injection, USP

PHARMACY BULK PACKAGE

NOT FOR DIRECT INFUSION

300 grams [THREE HUNDRED GRAMS] per Pharmacy Bulk Package Bag

FOR INTRAVENOUS USE ONLY

NOT TO BE DISPENSED AS A UNIT

Rx Only